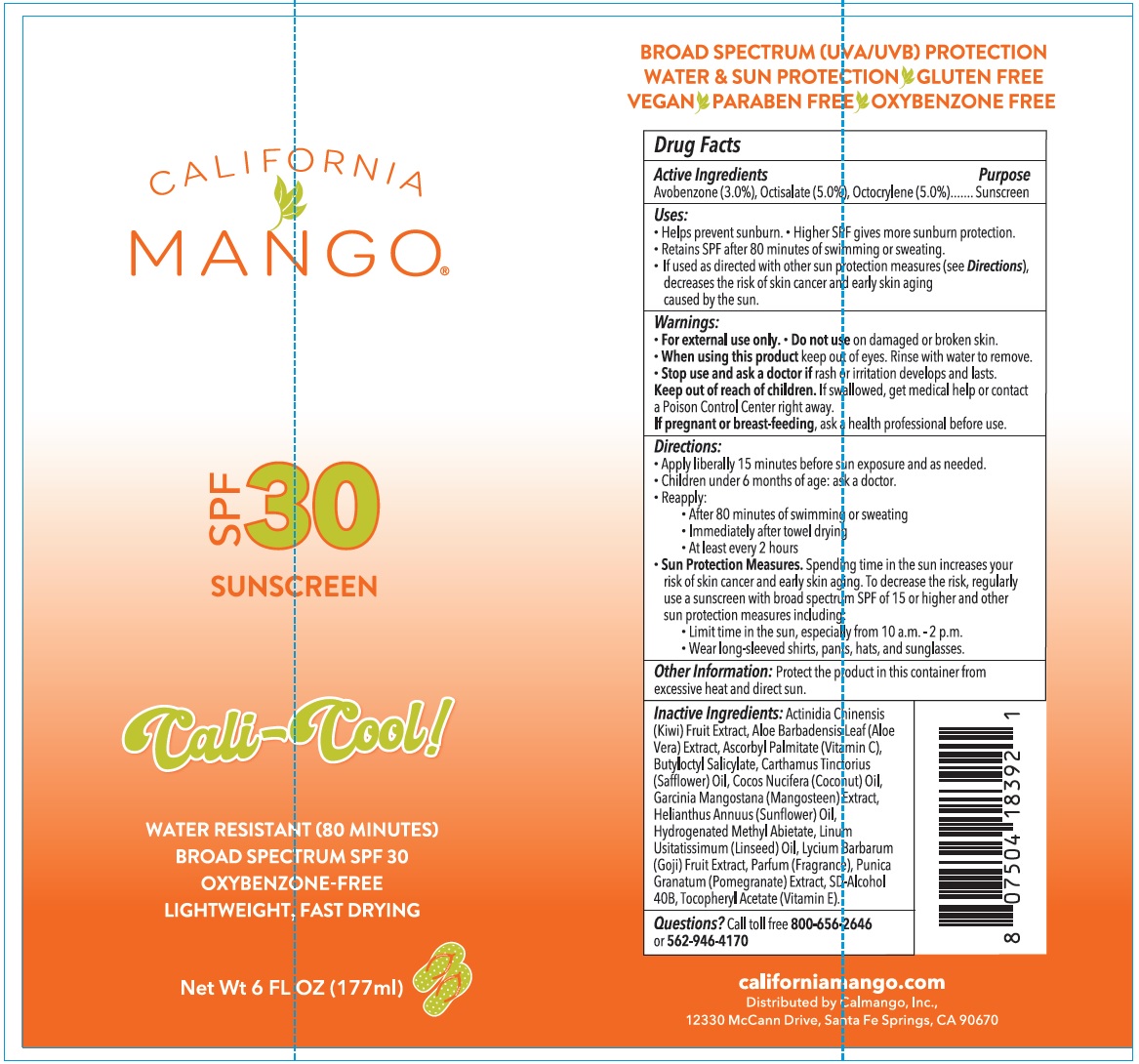 DRUG LABEL: CALIFORNIA MANGO SPF-30 SUNSCREEN
NDC: 83453-405 | Form: LIQUID
Manufacturer: CALMANGO, INC
Category: otc | Type: HUMAN OTC DRUG LABEL
Date: 20231106

ACTIVE INGREDIENTS: AVOBENZONE 30 mg/1 mL; OCTISALATE 50 mg/1 mL; OCTOCRYLENE 50 mg/1 mL
INACTIVE INGREDIENTS: KIWI FRUIT; ALOE VERA LEAF; ASCORBYL PALMITATE; BUTYLOCTYL SALICYLATE; SAFFLOWER; COCONUT OIL; HELIANTHUS ANNUUS FLOWERING TOP; HYDROGENATED METHYL ABIETATE; FLAX SEED; LYCIUM BARBARUM FRUIT; PUNICA GRANATUM ROOT BARK; .ALPHA.-TOCOPHEROL ACETATE

CALIFORNIA MANGO SPF-30 SUNSCREEN

Active Ingredients

Avobenzone (3.0%), Octisalate (5.0%), Octocrylene (5.0%)

Purpose

Sunscreen

Uses:

- Helps prevent sunburn.
- Higher SPF gives more sunburn protection.
- Retains SPF after 80 minutes of swmming or sweating.
- If used as directed with other sun protection measures (see), decreases the risk of skin cancer and early skin aging caused by the sun. Directions

Warnings:

For external use only.

Do not use

- on damaged or broken skin.

When using this product

- keep out of eyes. Rinse with water to remove.

Stop use and ask a doctor if

- rash or irritation develops and lasts.

Keep out of reach of children.

If swallowed, get medical help or contact a Poison Control Center right away.

If pregnant or breast-feeding,

ask a health professional before use.

Directions:

- Apply liberally 15 minutes before sun exposure and as needed.
- Children under 6 months of age: ask a doctor.
- Reapply:
- After 80 minutes of swimming or sweating
- Immediately after towel drying
- At least every 2 hours
- Sun Protection Measures. Spending time in the sun increases your risk of skin cancer and early skin aging. To decrease the risk, regularly use a suncreen with broad spectrum SPF of 15 or higher and other sun protection measures including:
- Limit time in the sun, especially from 10 a.m. - 2 p.m.
- Wear long-sleeved shirts, pants, hats, and sunglasses.

Other Information:

Protect the product in this container from excessive heat and direct sun.

Inactive Ingredients:

Actinidia Chinensis (Kiwi) Fruit Extract, Aloe Barbadensis Leaf (Aloe Vera) Extract, Ascorbyl Palmitate (Vitamin C), Butyloctyl Salicylate, Carthamus Tinctorius (Safflower) Oil, Cocos Nucifera (Coconut) Oil, Garcinia Mangostana (Mangosteen) Extract, Helianthus Annuus (Sunflower) Oil, Hydrogenated Methyl Abietate, Linum Usitatissimum (Linseed) Oil, Lycium Barbarum (Goji) Fruit Extract, Parfum (Fragrance), Punica Granatum (Pomegranante) Extract, SD-Alcohol 40B, Tocopheryl Acetate (Vitamin E).

Questions?

Call toll free or 800-656-2646562-946-4170